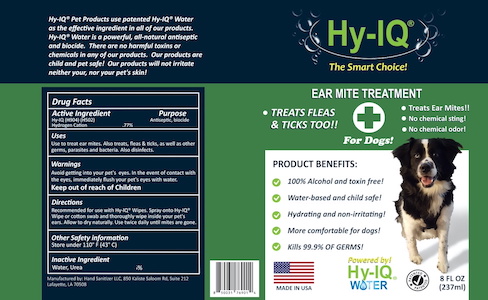 DRUG LABEL: HY IQ EAR MITE TREATMENT FOR DOGS
NDC: 76701-211 | Form: SPRAY
Manufacturer: HAND SANITIZER LLC
Category: animal | Type: OTC ANIMAL DRUG LABEL
Date: 20210624

ACTIVE INGREDIENTS: HYDROGEN CATION 10 mg/1 mL
INACTIVE INGREDIENTS: WATER 940 mg/1 mL; UREA 50 mg/1 mL

HY IQ EAR MITE TREATMENT FOR DOGS

ACTIVE INGREDIENTS

HY-IQ WATER ([H904] | [H502])

HYDROGEN CATION .77%

PURPOSE

ANTISEPTIC

USES

USE TO TREAT EAR MITES. ALSO TREATS FLEAS & TICKS, AS WELL AS OTHER GERMS, PARASITES AND BACTERIA. ALSO DISINFECTS.

WARNINGS

AVOID GETTING INTO YOUR PET'S EYES. IN THE EVENT OF CONTACT WITH THE EYES, IMMEDIATELY FLUSH YOUR PETS'S EYES WITH WATER.

KEEP OUT OF REACH OF CHILDREN

DIRECTIONS

RECOMMENDED FOR US WITH HY-IQ® WIPES. SPRAY ONTO HY-IQ® WIPE OR COTTON SWAB AND THROROUGHLY WIPE INSIDE YOUR PET'S EARS. ALLOW TO DRY NATURALLY. USE TWICE DAILY UNTIL MITES ARE GONE.

OTHER SAFETY INFORMATION

STORE UNDER 110°F (43°C)

INACTIVE INGREDIENTS

WATER, UREA